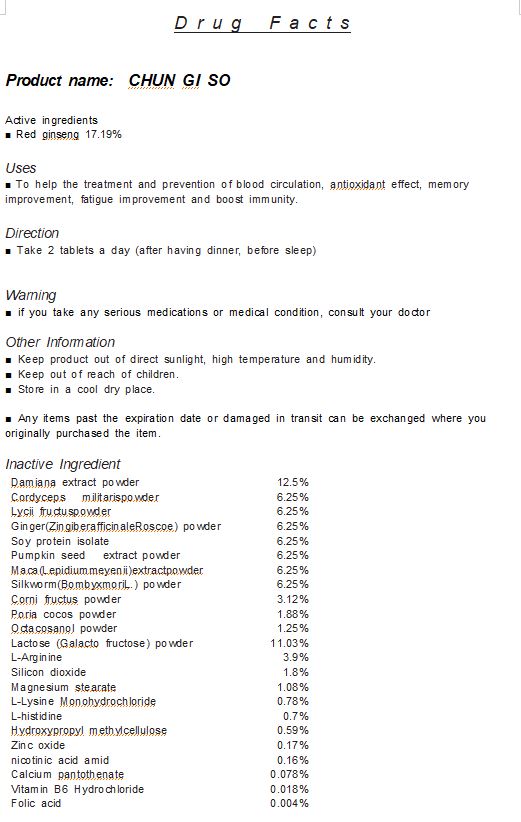 DRUG LABEL: Chun Gi So
NDC: 73426-0002 | Form: TABLET
Manufacturer: CHO WELL GF
Category: otc | Type: HUMAN OTC DRUG LABEL
Date: 20191122

ACTIVE INGREDIENTS: PANAX GINSENG WHOLE 17.19 g/100 g
INACTIVE INGREDIENTS: WOLFIPORIA COCOS WHOLE; CORDYCEPS MILITARIS WHOLE

Drug Facts

ACTIVE INGREDIENT

red ginseng

INACTIVE INGREDIENT

Damiana extract powder
Cordyceps militarispowder
Lycii fructuspowder
Ginger(ZingiberafficinaleRoscoe) p。wder
Soy protein isolate
Pumpkin seed extract powder
Maca(Lepidiummeyenii)extractpowder
Silkworm(Bombyxmoril.) powder
Corni fructus powder
Poria c。cos powder
Octacosanol powder
Lactose (Galacto fruct。se) powder
L-Arginine
Silicon di。xide
Magnesium stearate
L-Lysine Monohydrochloride
L-histidine
Hydr。xypropyl methylcellulose
Zinc oxide
nicotinic acid amid
Calcium pantothenate
Vitamin 86 Hydrochloride
Folic acid

PURPOSE

o help the treatment and prevention of blood circulation, antioxidant effect, memory improvement, fatigue improvement and boost immunity.

keep out of reach of the children

INDICATIONS AND USAGE

Take 2 tablets a day (after having dinner, before sleep)

WARNINGS

if you take any serious medications or medical condition, consult your doctor

DOSAGE AND ADMINISTRATION

for oral use only